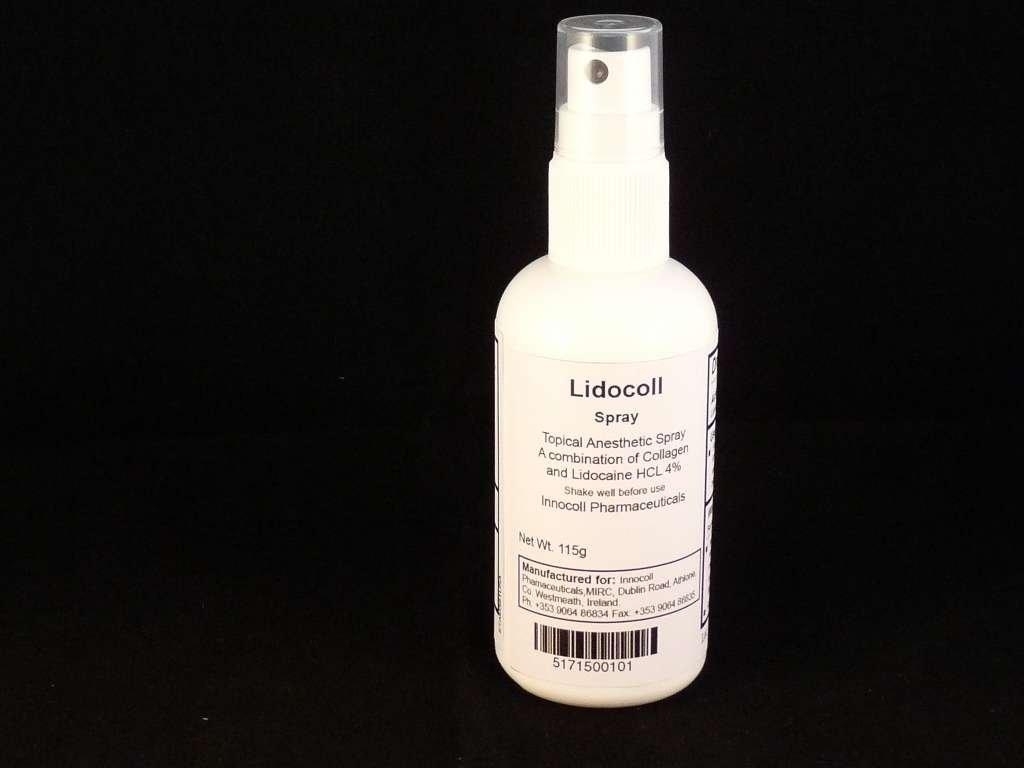 DRUG LABEL: Lidocoll
NDC: 51715-001 | Form: SPRAY
Manufacturer: Innocoll Pharmaceuticals
Category: otc | Type: HUMAN OTC DRUG LABEL
Date: 20111229

ACTIVE INGREDIENTS: Lidocaine Hydrochloride 4.6 g/115 g
INACTIVE INGREDIENTS: Water; Benzethonium Chloride 115 mg/115 g; Hydrochloric Acid 100 mg/115 g; Fish 17.25 g/115 g

Drug Facts

ACTIVE INGREDIENT

Lidocaine HCl 4%...............Anesthetic

Purpose

Anasthetic

Warning

Keep out of reach of children

Use

For the temporary relief of pain and
itching associated with minor burns,
sunburn, minor cuts, scrapes, insect
bites or minor skin irritations.

Warning

Avoid contact with eyes. If condition
worsens, or if symptoms persist for
more than 7 days or clear up and
occur again within a few days,
discontinue use and consult a doctor.
Keep out of reach of children.

Directions

Adults and children 2 years of age
and older: Apply Lidocoll spray not
more than 3 to 4 times per day or
moisten dressing prior to removal
to reduce pain.
Children under 2 years of age
consult a doctor.

Inactive Ingredients

hydrolyzed fish collagen (15%),
purified water, benzethonium
chloride and HCl.